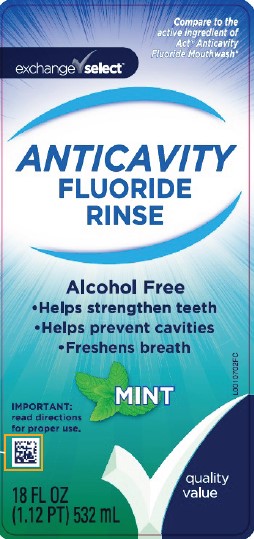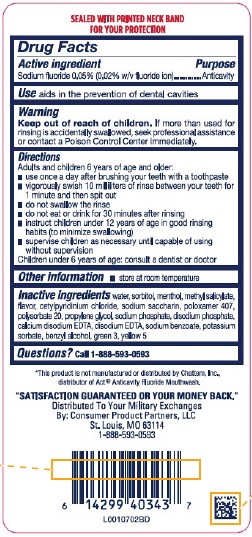 DRUG LABEL: Anticavity Fluoride Rinse
NDC: 55301-213 | Form: MOUTHWASH
Manufacturer: Your Military Exchanges
Category: otc | Type: HUMAN OTC DRUG LABEL
Date: 20260212

ACTIVE INGREDIENTS: SODIUM FLUORIDE 0.2 mg/1 mL
INACTIVE INGREDIENTS: WATER; SORBITOL; MENTHOL, UNSPECIFIED FORM; METHYL SALICYLATE; CETYLPYRIDINIUM CHLORIDE; SACCHARIN SODIUM; POLOXAMER 407; POLYSORBATE 20; PROPYLENE GLYCOL; SODIUM PHOSPHATE; SODIUM PHOSPHATE, DIBASIC, ANHYDROUS; EDETATE CALCIUM DISODIUM ANHYDROUS; EDETATE DISODIUM; SODIUM BENZOATE; POTASSIUM SORBATE; BENZYL ALCOHOL; FD&C GREEN NO. 3; FD&C YELLOW NO. 5

Exchange Select 213.002/213AE Rev 2
Anticavity Fluoride Rinse, Mint

Tamper Evident Statement

SEALED WITH PRINTED NECK BAND FOR YOUR PROTECTION

Active ingredient

Sodium fluoride 0.05% (0.02% w/v fluoride ion)

Purpose

Anticavity

Use

aids in the prevention of dental cavities

Warning

for this product

Keep out of reach of children.

If more than used for rinsing is accidentally swallowed, seek professional assistance or contact a Poison Control Center immediately.

Directiions

Adults and children 6 years of age and older:

- use once a day after brushing your teeth with a toothpaste
- vigorously swish 10 milliliters of rinse between your teeth for 1 minute then spit out
- do not swallow the rinse
- do not eat or drink for 30 minutes after rinsing
- instruct children under 12 years of age in good rinsing habits (to minimize swallowing)
- supervise children as necessary until capable of using without supervision

Children under 6 years of age: consult a dentist or doctor

Other information

- store at room temperature

Inactive ingredients

water, sorbitol, menthol, methyl salicylate, flavor, cetylpyridinium chloride, sodium saccharin, poloxamer 407, polysorbate 20, propylene glycol, sodium phosphate, disodium phosphate, calcium disodium EDTA, disodium EDTA, sodium benzoate, potassium sorbate, benzyl alcohol, green 3, yellow 5

Questions?

Call 1-888-593-0593

Disclaimer

*This product is not manufactured or distributed by Chattem, Inc, distributor of ACT®Anticavity Fluoride Mouthwash.

Adverse reactions

"SATISFACTION GUARANTEED OR YOUR MONEY BACK."

Distributed To Your Military Exchange

By: Consumer Product Partners, LLC

St. Louis, MO 63114

1-888-593-0593

Principal display panel

Exchange Select™

Compare to active ingredient of Act®Anticavity Fluoride Mouthwash*

ANTICAVITY

FLUORIDE RINSE

Alcohol free

- Helps strengthen teeth
- Helps prevent cavities
- Freshens breath

MINT

IMPORTANT: read directions for proper use.

quality value

18 FL OZ (1.12 PT) 532 mL